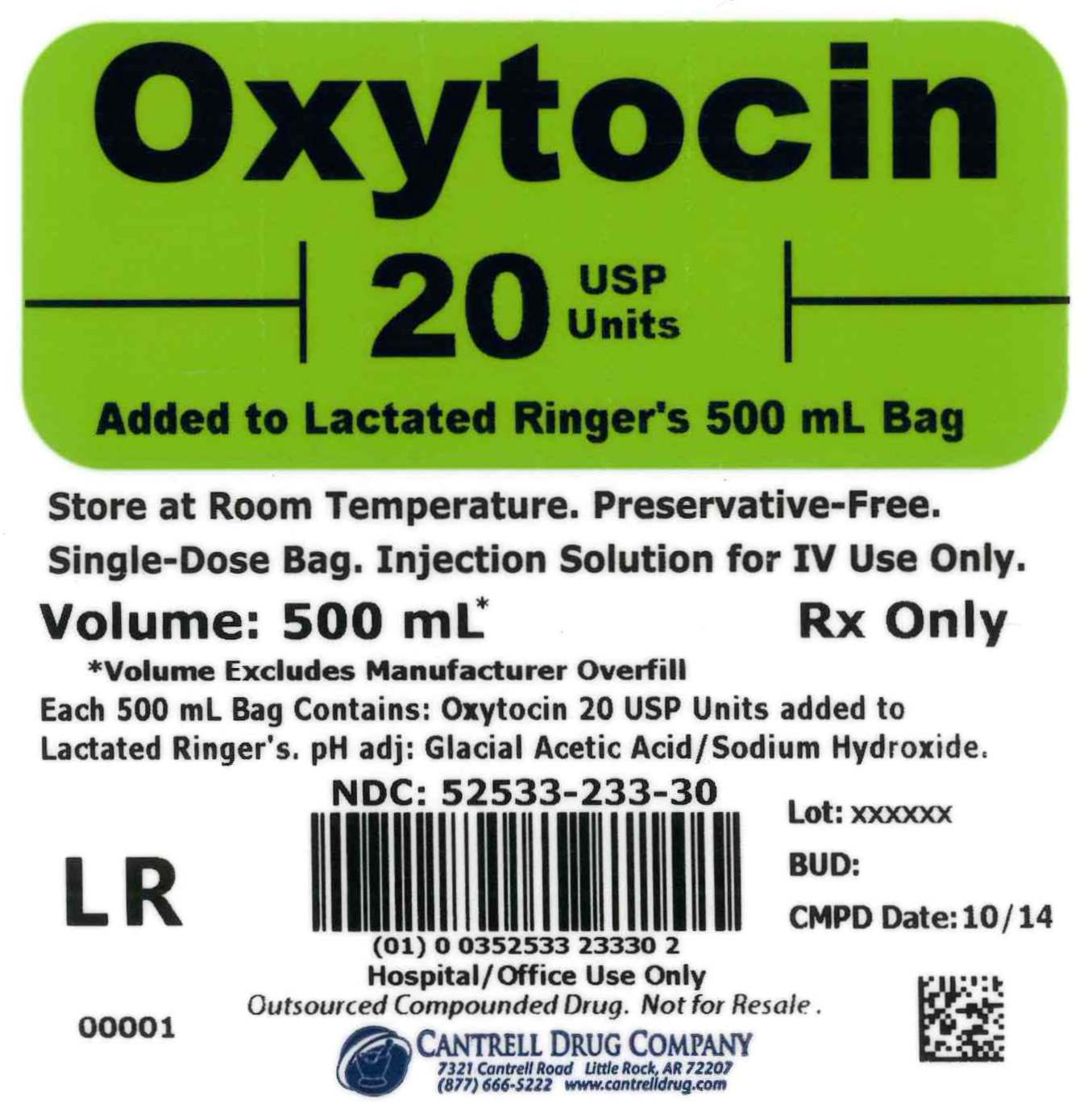 DRUG LABEL: Oxytocin
NDC: 52533-233 | Form: INJECTION, SOLUTION
Manufacturer: Cantrell Drug Company
Category: prescription | Type: HUMAN PRESCRIPTION DRUG LABEL
Date: 20160318

ACTIVE INGREDIENTS: OXYTOCIN 20 [USP'U]/500 mL
INACTIVE INGREDIENTS: SODIUM CHLORIDE 3 g/500 mL; SODIUM LACTATE 1.55 g/500 mL; POTASSIUM CHLORIDE 0.15 g/500 mL; CALCIUM CHLORIDE 0.1 g/500 mL; WATER

Oxytocin 20 USP Units Added to Lactated Ringer's 500 mL Bag